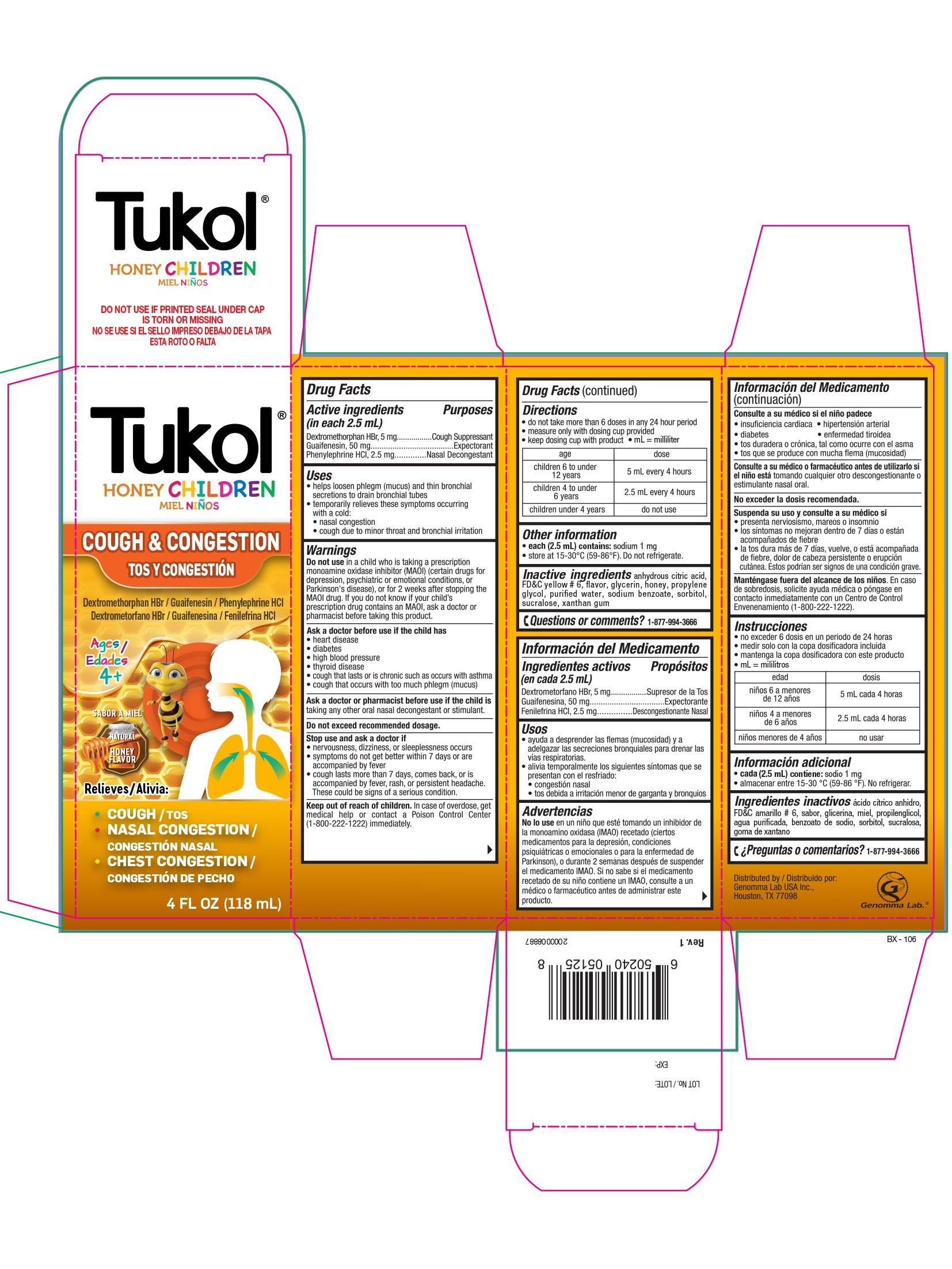 DRUG LABEL: Tukol Honey Children Cough and Congestion
NDC: 50066-301 | Form: SYRUP
Manufacturer: Genomma Lab USA
Category: otc | Type: HUMAN OTC DRUG LABEL
Date: 20241018

ACTIVE INGREDIENTS: DEXTROMETHORPHAN HYDROBROMIDE 5 mg/2.5 mL; GUAIFENESIN 50 mg/2.5 mL; PHENYLEPHRINE HYDROCHLORIDE 2.5 mg/2.5 mL
INACTIVE INGREDIENTS: ANHYDROUS CITRIC ACID; FD&C YELLOW NO. 6; HONEY; SODIUM BENZOATE; WATER; GLYCERIN; PROPYLENE GLYCOL; SORBITOL; XANTHAN GUM; SUCRALOSE

Tukol®Honey Children Cough & Congestion

Drug Facts

ACTIVE INGREDIENT

Active ingredients (in each 2.5 mL) | Purpose
Dextromethorphan HBr, 5 mg | Cough suppressant
Guaifenesin, 50 mg | Expectorant
Phenylephrine HCl, 2.5 mg | Nasal decongestant

Uses

- helps loosen phlegm (mucus) and thin bronchial secretions to drain bronchial tubes
- temporarily relieves these symptoms occurring with a cold:
  - nasal congestion
  - cough due to minor throat and bronchial irritation

Warnings

Do not use in a childwho is taking a prescription monoamine oxidase inhibitor (MAOI) (certain drugs for depression, psychiatric or emotional conditions, or Parkinson's disease), or for 2 weeks after stopping the MAOI drug. If you do not know if your child's prescription drug contains an MAOI, ask a doctor or pharmacist before taking this product.

Ask a doctor before use if the child has

- heart disease
- diabetes
- high blood pressure
- thyroid disease
- cough that lasts or is chronic such as occurs with asthma
- cough that occurs with too much phlegm (mucus)

Ask a doctor or pharmacist before use if the child istaking any other oral nasal decongestant or stimulant.

WHEN USING

Do not exceed recommended dosage.

Stop use and ask a doctor if

- nervousness, dizziness, or sleeplessness occurs
- symptoms do not get better within 7 days or are accompanied by fever
- cough lasts more than 7 days, comes back, or is accompanied by fever, rash, or persistent headache. These could be signs of a serious condition.

Keep out of reach of children.In case of overdose, get medical help or contact a Poison Control Center (1-800-222-1222) immediately.

Directions

- do not exceed 6 doses in a 24-hour period
- measure only with dosing cup provided
- keep dosing cup with product
- mL = mililiter

age | dose
children 6 to under 12 years | 5 mL every 4 hours
children 4 to under 6 years | 2.5 mL every 4 hours
children under 4 years | do not use

Other information

- each 2.5 mL contains: sodium 1 mg
- store at 15-30ºC (59-86ºF). Do not refrigerate.

Inactive ingredients

anhydrous citric acid, FD&C yellow # 6, flavor, glycerin, honey, propylene glycol, purified water, sodium benzoate, sorbitol, sucralose, xanthan gum

Questions or comments?

1-877-994-3666

Distributed by:
Genomma Lab USA Inc.,
Houston, TX 77098

PRINCIPAL DISPLAY PANEL - 118 ml Bottle Carton

Tukol®

HONEY CHILDREN

COUGH & CONGESTION

Dextromethorphan HBr / Guaifenesin / Phenylephrine HCl

Ages
4+

NATURAL

HONEY
FLAVOR

Relieves:

- COUGH
- NASAL CONGESTION
- CHEST CONGESTION

4 FL OZ (118 ml)